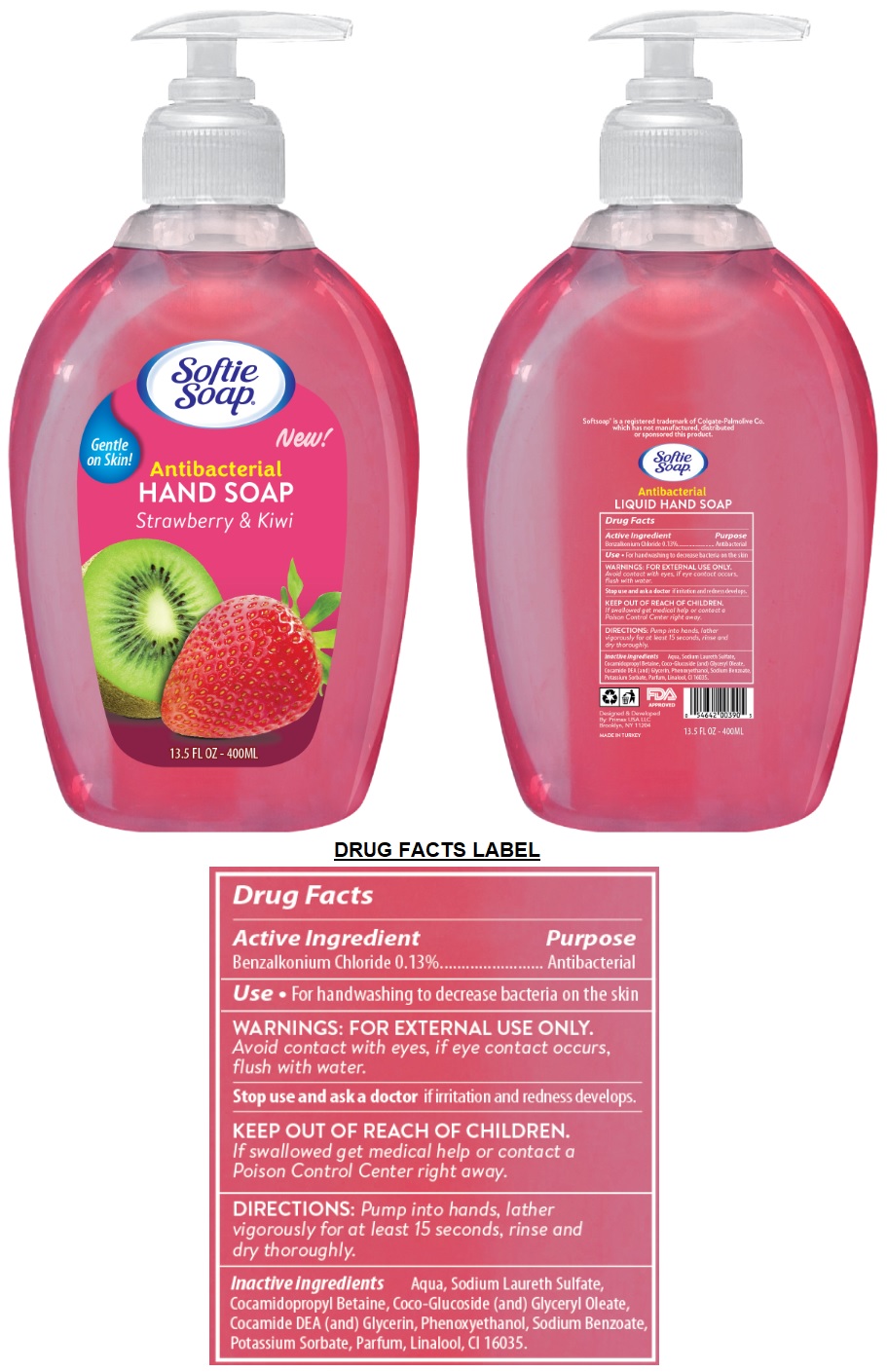 DRUG LABEL: Softie Antibacterial HANDSOAP Strawberry and Kiwi
NDC: 74955-053 | Form: LIQUID
Manufacturer: COSMOLIVE KOZMETIK SANAYI VE TICARET ANONIM SIRKETI
Category: otc | Type: HUMAN OTC DRUG LABEL
Date: 20210127

ACTIVE INGREDIENTS: BENZALKONIUM CHLORIDE 0.13 g/100 mL
INACTIVE INGREDIENTS: WATER; SODIUM LAURETH-3 SULFATE; COCAMIDOPROPYL BETAINE; COCO GLUCOSIDE; GLYCERYL OLEATE; COCO DIETHANOLAMIDE; GLYCERIN; PHENOXYETHANOL; SODIUM BENZOATE; POTASSIUM SORBATE; LINALOOL, (+/-)-; FD&C RED NO. 40

Softie Soap® Antibacterial HAND SOAP Strawberry & Kiwi

Active Ingredient

Benzalkonium Chloride 0.13%

Purpose

Antibacterial

Use

• For handwashing to decrease bacteria on the skin

WARNINGS:

FOR EXTERNAL USE ONLY.

Avoid contact with eyes, if eye contact occurs, flush with water.

Stop use and ask a doctor if irritation and redness develops.

KEEP OUT OF REACH OF CHILDREN.

If swallowed get medical help or contact a Poison Control Center right away.

DIRECTIONS:

Pump into hands, lather vigorously for at least 15 seconds, rinse and dry thoroughly.

Inactive ingredients

Aqua, Sodium Laureth Sulfate, Cocamidopropyl Betaine, Coco-Glucoside (and) Glyceryl Oleate, Cocamide DEA (and) Glycerin, Phenoxyethanol, Sodium Benzoate, Potassium Sorbate, Parfum, Linalool, CI 16035.

Gentle on Skin!

New!

Softsoap® is a registered trademark of Colgate-Palmolive Co. which has not manufactured, distributed or sponsored this product.

FDA APPROVED

Designed & Developed

By: Primax USA LLC

Brooklyn, NY 11204

MADE IN TURKEY